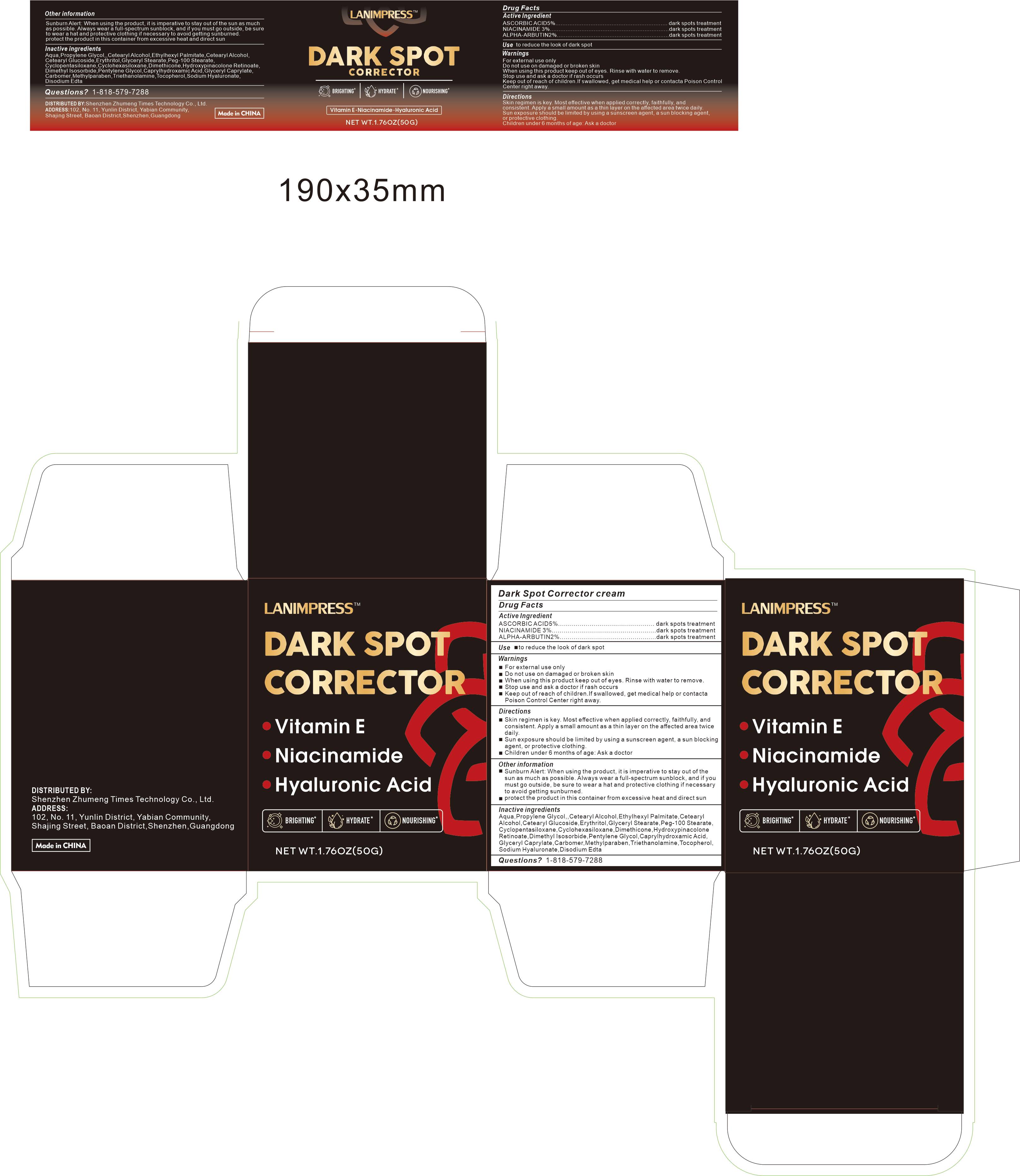 DRUG LABEL: LANIMPRESS Dark Spot Corrector cream
NDC: 84372-025 | Form: LIQUID
Manufacturer: Shenzhen Zhumeng Times Technology Co., Ltd.
Category: otc | Type: HUMAN OTC DRUG LABEL
Date: 20240826

ACTIVE INGREDIENTS: NIACINAMIDE 3 g/50 g; ASCORBIC ACID 1 g/50 g; ALPHA-ARBUTIN 2 g/50 g
INACTIVE INGREDIENTS: METHYLPARABEN; GLYCERYL MONOSTEARATE; TOCOPHEROL; CETOSTEARYL ALCOHOL; CETEARYL GLUCOSIDE; TROLAMINE; PEG-100 STEARATE; CYCLOMETHICONE 5; DIMETHICONE; HYALURONATE SODIUM; GLYCERYL DISTEARATE; ERYTHRITOL; APPLE; ELASTIN (HUMAN); WATER; PROPYLENE GLYCOL; ETHYLHEXYL PALMITATE; HYDROXYPROLINE; CYCLOMETHICONE 6; CAPRYLHYDROXAMIC ACID

Active ingredients

ASCORBIC ACID5%....... dark spots treatment

NIACINAMIDE 3%...... dark spots treatment

ALPHA-ARBUTIN2%....dark spots treatment

Purpose

To help smooth the look of wrinkles, even skin tone

Uses

Smooth evenly over your cleansed face and neck morning and night.

Contraindications, Precautions, Warnings, and Instructions

For external use only

Do not use on damaged or broken skin

When using this product keep out of eyes. Rinse with water to remove.

Stop use and ask a doctor if rash occurs

Keep out of reach of children.lf swallowed, get medical help or contact a Poison Control Center right away.

Dosage and administration

For external use only.

Do not use

Stop use and ask a doctor if rash occurs

When using section

When using this product keep out of eyes. Rinse with water to remove.

stop use

Do not use on open wounds or allergic skin.

Keep out of reach of children.

If sxralowed, get medical help or contact a Poison Conirol Cenler ngiht away.

Inactive ingredients

AQUA,PROPYLENE GLYCOL,CETEARYL ALCOHOL,ETHYLHEXYL PALMITATE,MALUS DOMESTICA FRUIT EXTRACT,ELASTIN,HYDROXYPROLINE,CETEARYL ALCOHOL,CETEARYL GLUCOSIDE,ERYTHRITOL,GLYCERYL STEARATE,PEG-100 STEARATE,CYCLOPENTASILOXANE,CYCLOHEXASILOXANE,DIMETHICONE,HYDROLYZED COLLAGEN,PENTYLENE GLYCOL,CAPRYLHYDROXAMIC ACID,GLYCERYL CAPRYLATE,CARBOMER,METHYLPARABEN,TRIETHANOLAMINE,SODIUM HYALURONATE,TOCOPHEROL,NIACINAMIDE,DISODIUM EDTA